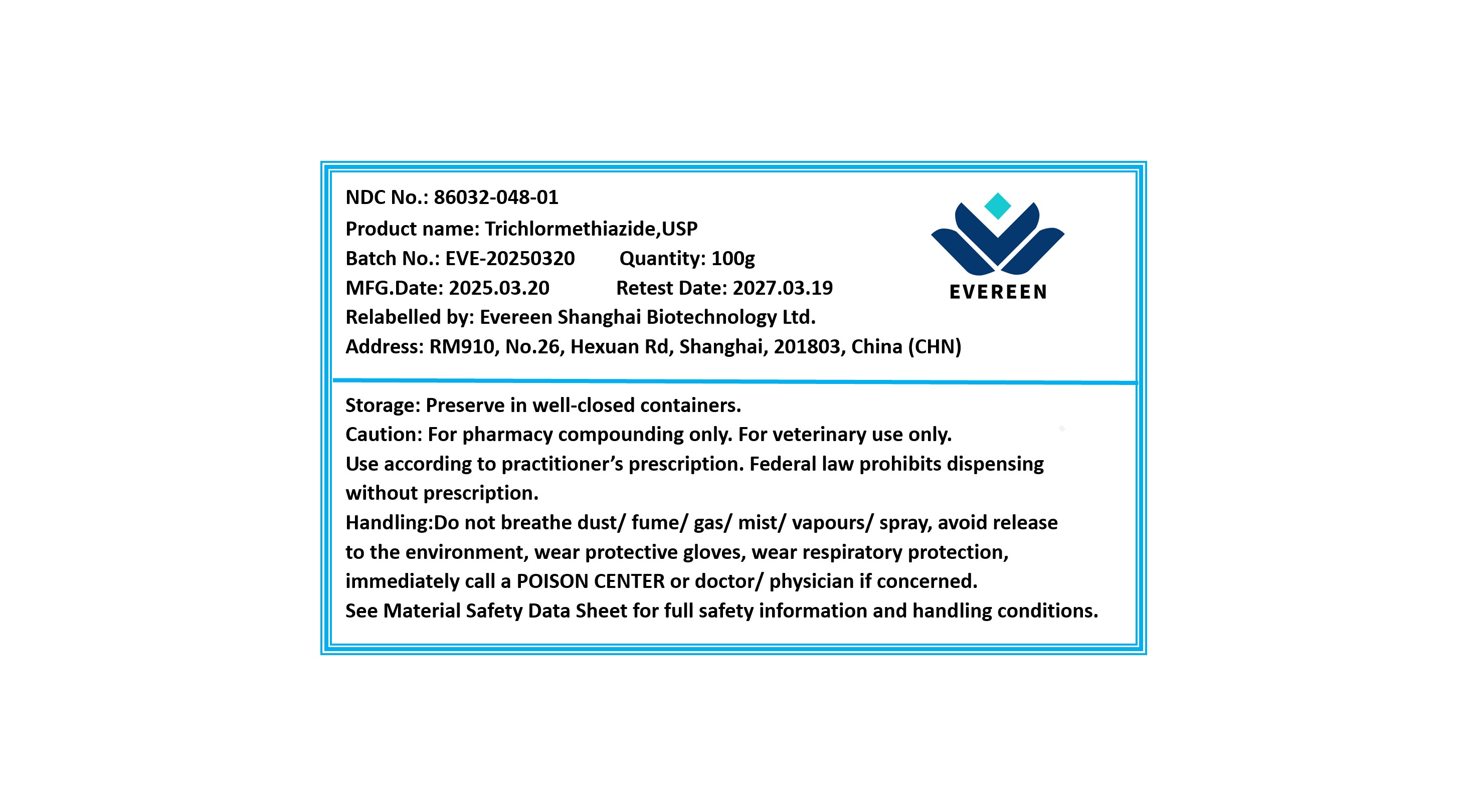 DRUG LABEL: Trichlormethiazide
NDC: 86032-048 | Form: POWDER
Manufacturer: Evereen Shanghai Biotechnology Ltd.
Category: other | Type: BULK INGREDIENT - ANIMAL DRUG
Date: 20250328

ACTIVE INGREDIENTS: TRICHLORMETHIAZIDE 1 g/1 g

Trichlormethiazide